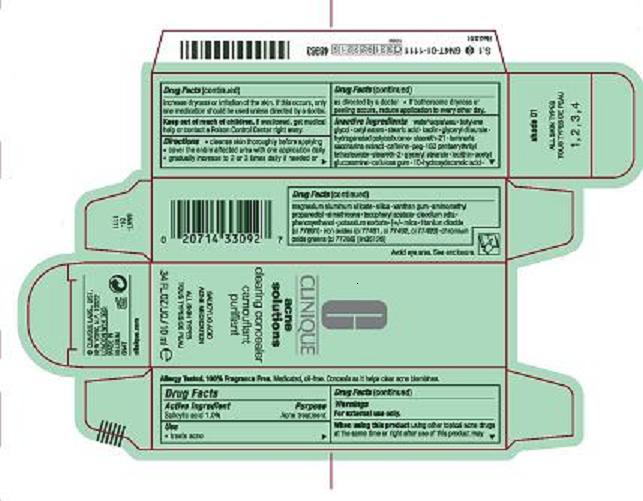 DRUG LABEL: ACNE SOLUTIONS CLEARING CONCEALER
NDC: 49527-749 | Form: LOTION
Manufacturer: CLINIQUE LABORATORIES INC
Category: otc | Type: HUMAN OTC DRUG LABEL
Date: 20100401

ACTIVE INGREDIENTS: SALICYLIC ACID 1.0 mL/100 mL

ACTIVE INGREDIENT: 1.0% SALICYLIC ACID

PURPOSE: ACNE TREATMENT

USE: TREATS ACNE

WARNINGS: FOR EXTERNAL USE ONLY. AVOID EYE AREA

WHEN USING THIS PRODUCT: USING OTHER TOPICAL ACNE DRUGS AT THE SAME TIME OR RIGHT AFTER USE OF THIS PRODUCT MAY INCREASE DRYNESS OR IRRITATION OF THE SKIN. IF THIS OCCURS, ONLY ONE MEDICATION SHOULD BE USED UNLESS DIRECTED BY A DOCTOR.

KEEP OUT OF REACH OF CHILDREN. IF SWALLOWED, GET MEDICAL HELP OR CONTACT A POISON CONTROL CENTER RIGHT AWAY.

DIRECTIONS

- CLEANSE SKIN THOROUGHLY BEFORE APPLYING
- COVER THE ENTIRE AFFECTED AREA WITH ONE APPLICATION
- GRADUALLY INCREASE TO 2 OR 3 TIMES DAILY IF NEEDED OR AS DIRECTED BY A DOCTOR
- IF BOTHERSOME DRYNESS OR PEELING OCCURS, REDUCE APPLICATION TO EVERY OTHER DAY.

INACTIVE INGREDIENT

INACTIVE INGREDIENTS: WATER , BUTYLENE GLYCOL , CETYL ESTERS , STEARIC ACID , KAOLIN , GLYCERYL DILAURATE , HYDROGENATED POLYISOBUTENE , STEARETH-21 , LAMINARIA SACCHARINA EXTRACT , CAFFEINE , PEG-150 PENTAERYTHRITYL TETRASTEARATE , STEARETH-2 , GLYCERYL STEARATE , LECITHIN , ACETYL GLUCOSAMINE , CELLULOSE GUM , 10-HYDROXYDECANOIC ACID , MAGNESIUM ALUMINUM SILICATE, , SILICA , XANTHAN GUM , AMINOMETHYL PROPANEDIOL , SIMETHICONE , TOCOPHERYL ACETATE , DISODIUM EDTA , PHENOXYETHANOL , POTASSIUM SORBATE MAY CONTAIN: MICA, TITANIUM DIOXIDE, IRON OXIDES, CHROMIUM OXIDE GREENS ILN35126

PACKAGE LABEL

PRINCIPLE DISPLAY PANEL 0.34 FL OZ LIQ CARTON
CLINIQUE ACNE SOLUTIONS CLEARING CONCEALER
SALICYLIC ACID ACNE MEDICATION
ALL SKIN TYPES
.34 FL OZ/ 10 mL
CLINIQUE LABS DISTR.
NEW YORK, NY 10022
CLINIQUE.COM